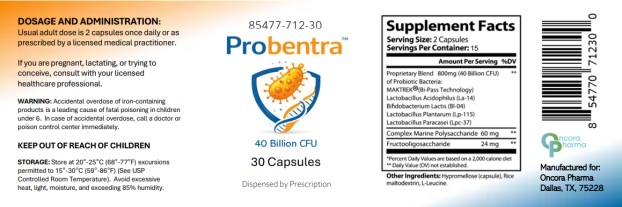 DRUG LABEL: Probentra
NDC: 85477-712 | Form: CAPSULE
Manufacturer: Oncora Pharma, LLC
Category: prescription | Type: HUMAN PRESCRIPTION DRUG LABEL
Date: 20260225

ACTIVE INGREDIENTS: LACTOBACILLUS ACIDOPHILUS LA 14 400 mg/1 1; BIFIDOBACTERIUM ANIMALIS LACTIS BL04 400 mg/1 1; LACTIPLANTIBACILLUS PLANTARUM 400 mg/1 1; LACTICASEIBACILLUS PARACASEI LPC-37 400 mg/1 1; LESSONIA NIGRESCENS 30 mg/1 1; BETA VULGARIS ROOT FRUCTOOLIGOSACCHARIDES 12 mg/1 1
INACTIVE INGREDIENTS: HYPROMELLOSE, UNSPECIFIED; MALTODEXTRIN; LEUCINE

Probentra

DESCRIPTION

Probentra™ is a prescription-dispensed oral probiotic dietary supplement formulated to support gastrointestinal health and maintain normal intestinal flora. Each serving (two capsules) delivers 40 billion colony-forming units (CFU) of beneficial probiotic organisms combined with marine polysaccharide and fructooligosaccharide (FOS).

The proprietary probiotic blend includes:

- Lactobacillus acidophilus (La-14®)
- Bifidobacterium lactis (Bl-04®)
- Lactobacillus plantarum (Lp-115®)
- Lactobacillus paracasei (Lpc-37®)

The formulation utilizes MAKTrek® Bi-Pass Technology to support probiotic viability during gastrointestinal transit.

Probentra™ is intended for use under the supervision of a licensed healthcare practitioner.

INDICATIONS AND USAGE

Probentra™ is indicated as a probiotic dietary supplement to support digestive health and promote balance of normal intestinal microflora.

It is dispensed by prescription and intended for use under medical supervision as part of a dietary supplementation plan.

(Notice: no disease treatment claims — this keeps you clean in Rx dietary supplement lane.)

DOSAGE AND ADMINISTRATION

Adults: Take two (2) capsules once daily, or as directed by a licensed healthcare practitioner.

CONTRAINDICATIONS

Probentra™ is contraindicated in individuals with known hypersensitivity to any of its ingredients.

WARNINGS AND PRECAUTIONS

- If pregnant, nursing, or attempting to conceive, consult a licensed healthcare professional prior to use.
- Keep out of reach of children.
- Accidental overdose of iron-containing products is a leading cause of fatal poisoning in children under six years of age. In case of accidental overdose, call a physician or poison control center immediately.

ADVERSE REACTIONS

Probiotic supplementation may occasionally result in mild gastrointestinal symptoms such as bloating, gas, or abdominal discomfort. If adverse reactions occur, discontinue use and consult a healthcare professional.

HOW SUPPLIED

Probentra™ (NDC 85477-712-30) is supplied in bottles of 30 capsules.

STORAGE

Store at 20°–25°C (68°–77°F); excursions permitted to 15°–30°C (59°–86°F).
Protect from excessive heat, moisture, and light.

Principal Display Panel

85477-712-30
Probentra
40 Billion CFU
30 Capsules
Dispensed by Prescription